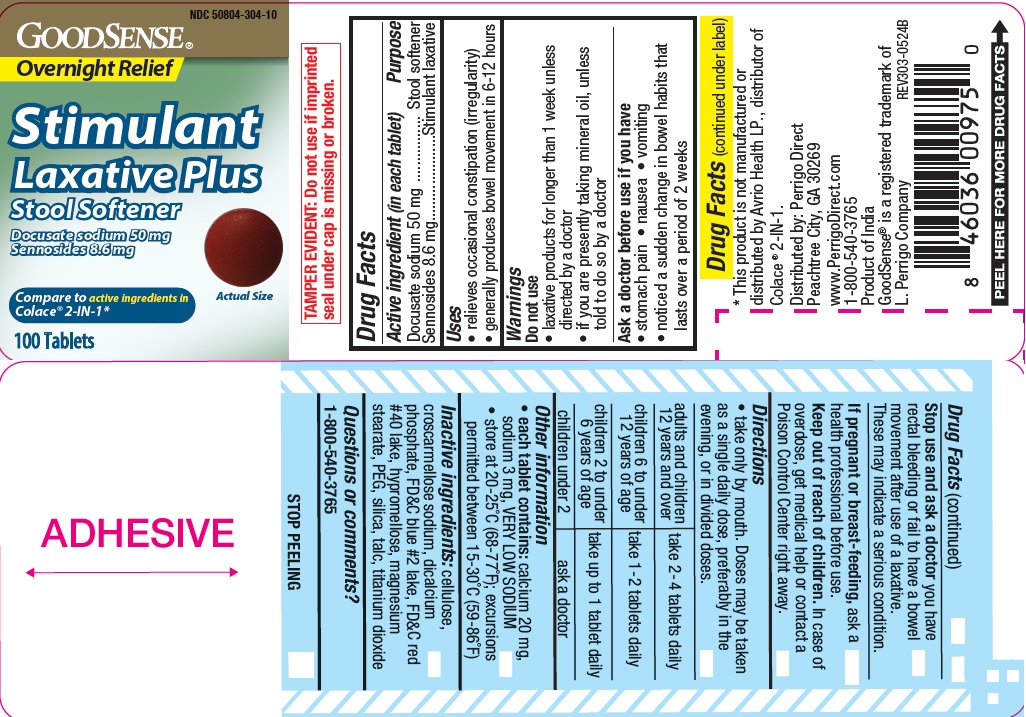 DRUG LABEL: Stimulant Laxative Plus Stool Softener
NDC: 50804-304 | Form: TABLET, FILM COATED
Manufacturer: GOOD SENSE
Category: otc | Type: HUMAN OTC DRUG LABEL
Date: 20240722

ACTIVE INGREDIENTS: SENNOSIDES 8.6 mg/1 1; DOCUSATE SODIUM 50 mg/1 1
INACTIVE INGREDIENTS: POLYETHYLENE GLYCOL, UNSPECIFIED; HYPROMELLOSES; FD&C BLUE NO. 2; TITANIUM DIOXIDE; MAGNESIUM STEARATE; CELLULOSE, MICROCRYSTALLINE; CROSCARMELLOSE SODIUM; CALCIUM PHOSPHATE, DIBASIC, DIHYDRATE; FD&C RED NO. 40; SILICON DIOXIDE; TALC

GS 303B (304)

Active ingredient (in each tablet)

Docusate Sodium 50 mg
Sennosides 8.6 mg

Purpose

Stool softener

Stimulant laxative

Uses

- relieves occasional constipation (irregularity)

- generally produces bowel movement in 6-12 hours

Warnings

Do not use

- laxative products for longer than 1 week unless directed by a doctor
- if you are presently taking mineral oil, unless told to do so by a doctor

Ask a doctor before use if you have

- stomach pain
- nausea
- vomiting
- noticed a sudden change in bowel habits that lasts over 2 weeks

Stop use and ask a doctor if you have rectal bleeding or fail to have a bowel movement after use of a laxative. These may indicate a serious condition.

If pregnant or breast-feeding, ask a health professional before use.

Keep out of reach of children. In case of overdose, get medical help or contact a Poison Control Center right away.

Directions

- Take only by mouth. Doses may be taken as a single daily dose, preferably in the evening, or in divided doses

adults and children 12 years and over | take 2-4 tablets daily
children 6 to under 12 years of age | take 1- 2 tablets daily
children 2 to under 6 years of age | take up to 1 tablet daily
children under 12 years of age | ask a doctor

Other information

- each tablet contains: calcium 20 mg, sodium 3 mg, VERY LOW SODIUM
- store at 20-25 C (68-77 F); excursions permitted between 15-30 C (59-86 F)

Inactive ingredients

cellulose, croscarmellose sodium, dicalcium phosphate, FD&C blue #2 lake, FD&C red #40 lake, hypromellose, magnesium stearate, PEG, silica, talc, titanium dioxide.

Questions or comments?

1-800-540-3765